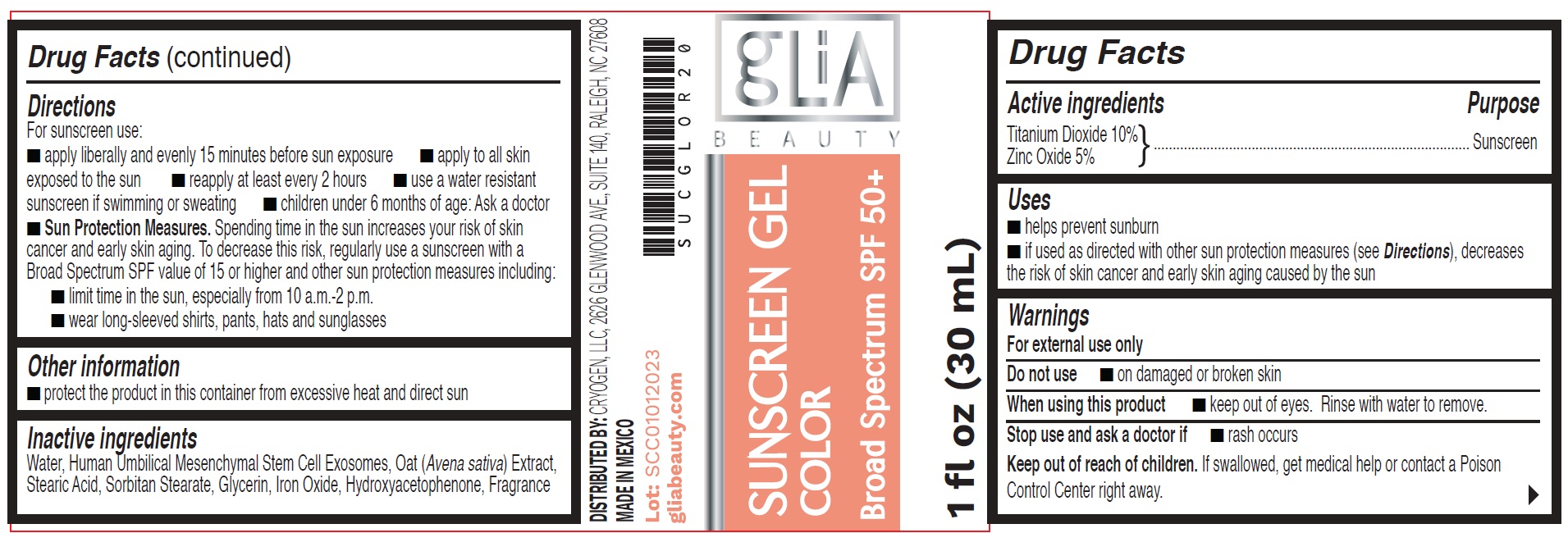 DRUG LABEL: Sunscreen Color Broad spectrum SPF 50
NDC: 83802-001 | Form: GEL
Manufacturer: CryoGen, LLC
Category: otc | Type: HUMAN OTC DRUG LABEL
Date: 20231117

ACTIVE INGREDIENTS: TITANIUM DIOXIDE 100 mg/1 mL; ZINC OXIDE 50 mg/1 mL
INACTIVE INGREDIENTS: WATER; OAT; STEARIC ACID; SORBITAN MONOSTEARATE; GLYCERIN; FERRIC OXIDE RED; HYDROXYACETOPHENONE

Sunscreen Gel Color Broad spectrum SPF 50+

Active ingredients

Titanium Dioxide 10%

Zinc Oxide 5%

Purpose

Sunscreen

Uses

- helps prevent sunburn
- if used as directed with other sun protection measures (see Directions), decreases the risk of skin cancer and early skin aging caused by the sun

Warnings

For external use only

Do not use

- on damaged or broken skin

When using this product

- keep out of eyes. Rinse with water to remove.

Stop use and ask a doctor if

- rash occurs

Keep out of reach of children.

If swallowed, get medical help or contact a Poison Control Center right away.

Directions

For sunscreen use:

- apply liberally and evenly 15 minutes before sun exposure
- apply to all skin exposed to the sun
- reapply at least every 2 hours
- use a water resistant sunscreen if swimming or sweating
- children under 6 months of age: Ask a doctor
- Sun Protection Measures.Spending time in the sun increases your risk of skin cancer and early skin aging. To decrease this risk, regularly use a sunscreen with a Broad Spectrum SPF value of 15 or higher and other sun protection measures including:
- limit time in the sun, especially from 10 a.m.-2 p.m.
- wear long-sleeved shirts, pants, hats and sunglasses

Other information

- protect the product in this container from excessive heat and direct sun

Inactive ingredients

Water, Human Umbilical Mesenchymal Stem Cell Exosomes, Oat (Avena sativa) Extract, Stearic Acid, Sorbitan Stearate, Glycerin, Iron Oxide, Hydroxyacetophenone, Fragrance